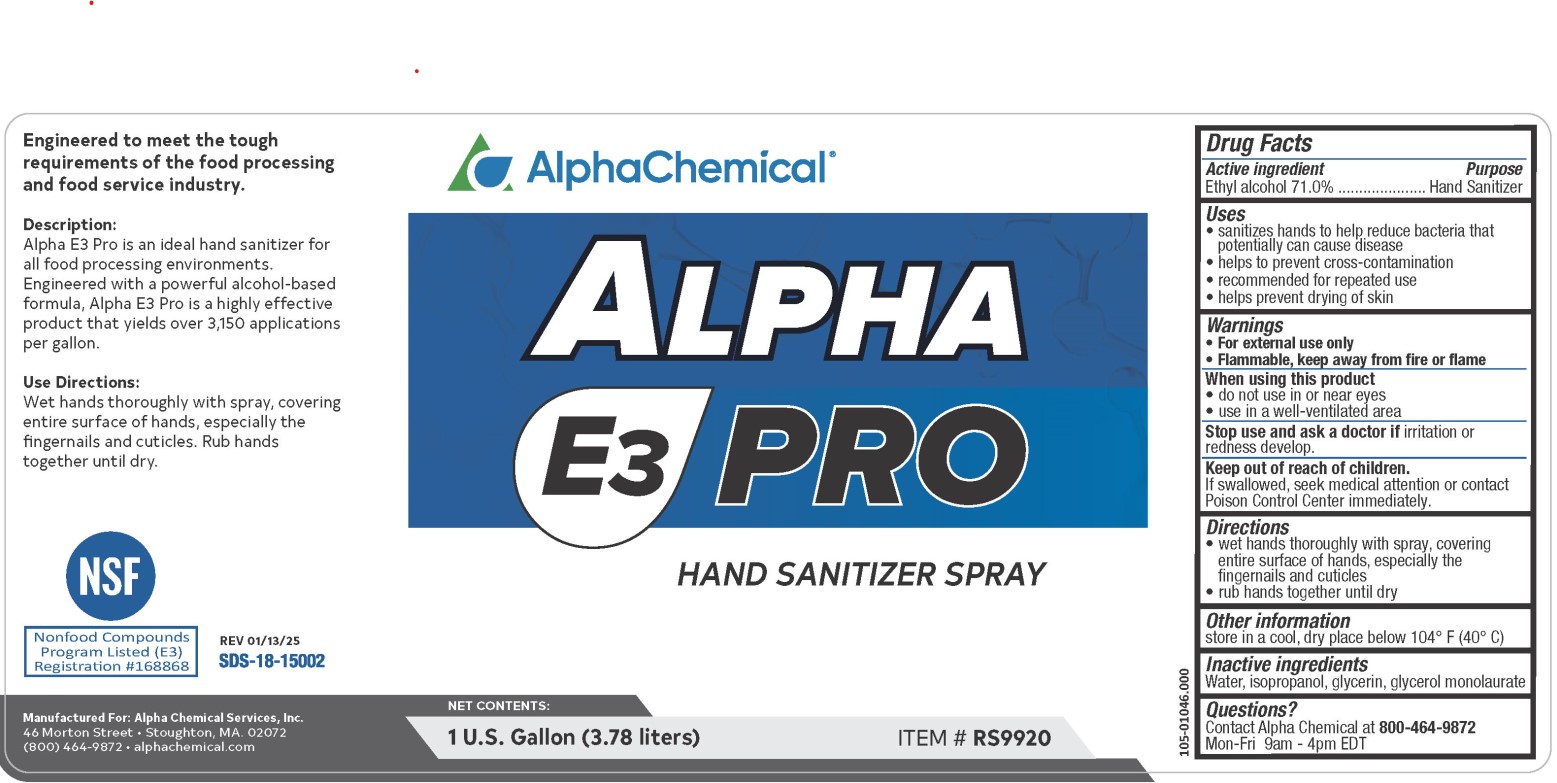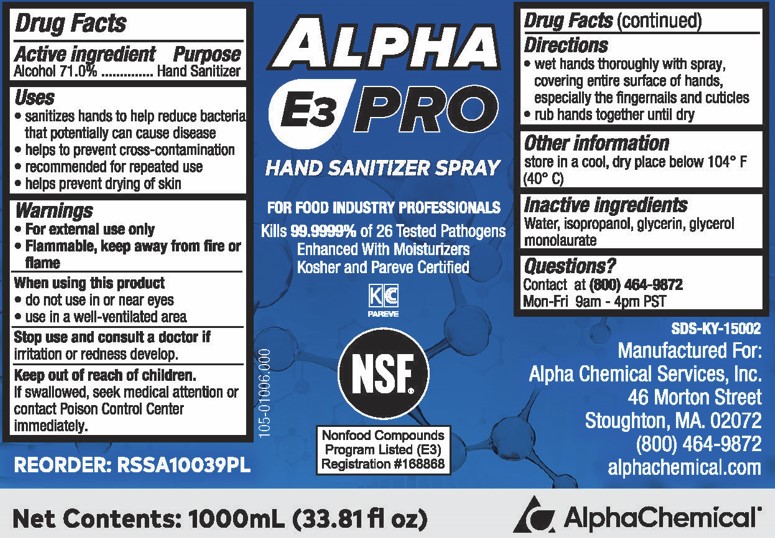 DRUG LABEL: Alpha E3 PRO Hand Sanitizer
NDC: 69335-005 | Form: SPRAY
Manufacturer: Alpha Chemical Services, Inc.
Category: otc | Type: HUMAN OTC DRUG LABEL
Date: 20250818

ACTIVE INGREDIENTS: ALCOHOL 71 mL/100 mL
INACTIVE INGREDIENTS: GLYCERYL LAURATE; WATER; ISOPROPYL ALCOHOL; GLYCERIN

ALPHA E3 PRO Hand Sanitizer Spray 69335-005

Active ingredient

Alcohol 71.0%

Purpose

Hand Sanitizer

Uses

- sanitizes hands to help reduce bacteria that potentially can cause disease
- helps to prevent cross-contamination
- recommended for repeated use
- helps prevent drying of skin

Warnings

- For external use only
- Flammable, keep away from fire or flame

When using this product

- do not use in or near eyes
- use in a well-ventilated area

Stop use and consult a doctor if

irritation or redness develop

Keep out of reach of children.

If swallowed, seek medical attention or contact Poison Control center immediately.

Directions

- wet hands thoroughly with spray, covering entire surface of hands, especially the fingernails and cuticles
- rub hands together until dry

Other information

store in a cool, dry place below 104° F (40° C)

Inactive ingredients

Water, isopropanol, glycerin, glycerol monolaurate

Questions?

Contact at (800) 464-9872

Mon-Fri 9 am - 4pm PST

PACKAGE LABEL

ALPHA

E3 PRO

HAND SANITIZER SPRAY

FOR FOOD INDUSTRY PROFESSIONALS

Kills 99.9999% of 26 Tested Pathogens

Enhanced With Moisturizers

Koser and Pareve Certified

KC

PAREVE

NSF

Nonfood Compunds

Program Listed (E3)

Registration #168868

Net Contents: 1000mL (33.81 fl oz)